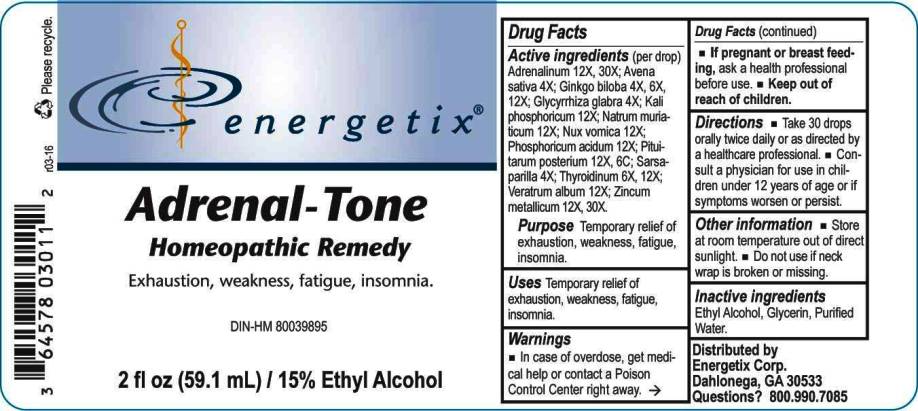 DRUG LABEL: Adrenal Tone
NDC: 64578-0121 | Form: LIQUID
Manufacturer: Energetix Corp
Category: homeopathic | Type: HUMAN OTC DRUG LABEL
Date: 20160407

ACTIVE INGREDIENTS: EPINEPHRINE 12 [hp_X]/1 mL; AVENA SATIVA FLOWERING TOP 4 [hp_X]/1 mL; GINKGO 4 [hp_X]/1 mL; GLYCYRRHIZA GLABRA 4 [hp_X]/1 mL; POTASSIUM PHOSPHATE, DIBASIC 12 [hp_X]/1 mL; SODIUM CHLORIDE 12 [hp_X]/1 mL; STRYCHNOS NUX-VOMICA SEED 12 [hp_X]/1 mL; PHOSPHORIC ACID 12 [hp_X]/1 mL; BOS TAURUS PITUITARY GLAND 12 [hp_X]/1 mL; SMILAX REGELII ROOT 4 [hp_X]/1 mL; THYROID, BOVINE 6 [hp_X]/1 mL; VERATRUM ALBUM ROOT 12 [hp_X]/1 mL; ZINC 12 [hp_X]/1 mL
INACTIVE INGREDIENTS: WATER; ALCOHOL; GLYCERIN

Drug Facts:

ACTIVE INGREDIENTS:

Adrenalinum 12X, 30X, Avena Sativa 4X, Ginkgo Biloba 4X, 6X, 12X, Glycyrrhiza Glabra 4X, Kali Phosphoricum 12X, Natrum Muriaticum 12X, Nux Vomica 12X, Phosphoricum Acidum 12X, Pituitarum Posterium (Bovine) 12X 6C, Sarsaparilla (Smilax Regelii) 4X, Thyroidinum (Bovine) 6X, 12X, Veratrum Album 12X, Zincum Metallicum 12X, 30X

PURPOSE:

Temporary relief of exhaustion, weakness, fatigue, insomnia.

WARNINGS:

In case of overdose, get medical help or contact a Poison Control Center right away.

If pregnant or breast feeding, ask a health professional before use.

Keep out of reach of children.

Other information
Store at room temperature out of direct sunlight.
Do not use if neck wrap is broken or missing.

Keep out of reach of children. In case of overdose, get medical help or contact a Poison Control Center right away.

DIRECTIONS:

Take 30 drops orally twice daily or as directed by a healthcare professional.

Consult a physician for use in children under 12 years of age or if symptoms worsen or persist.

USES:

Temporary relief of exhaustion, weakness, fatigue, insomnia.

INACTIVE INGREDIENTS:

Ethyl Alcohol, Glycerin, Purified Water

QUESTIONS:

Distributed by
Energetix Corp.
Dahlonega, GA 30533

Questions? 800.990.7085

PACKAGE LABEL DISPLAY:

energetix

Adrenal-Tone

Homeopathic Remedy

Exhaustion, weakness, fatigue, insomnia

2 fl oz (59.1 mL)